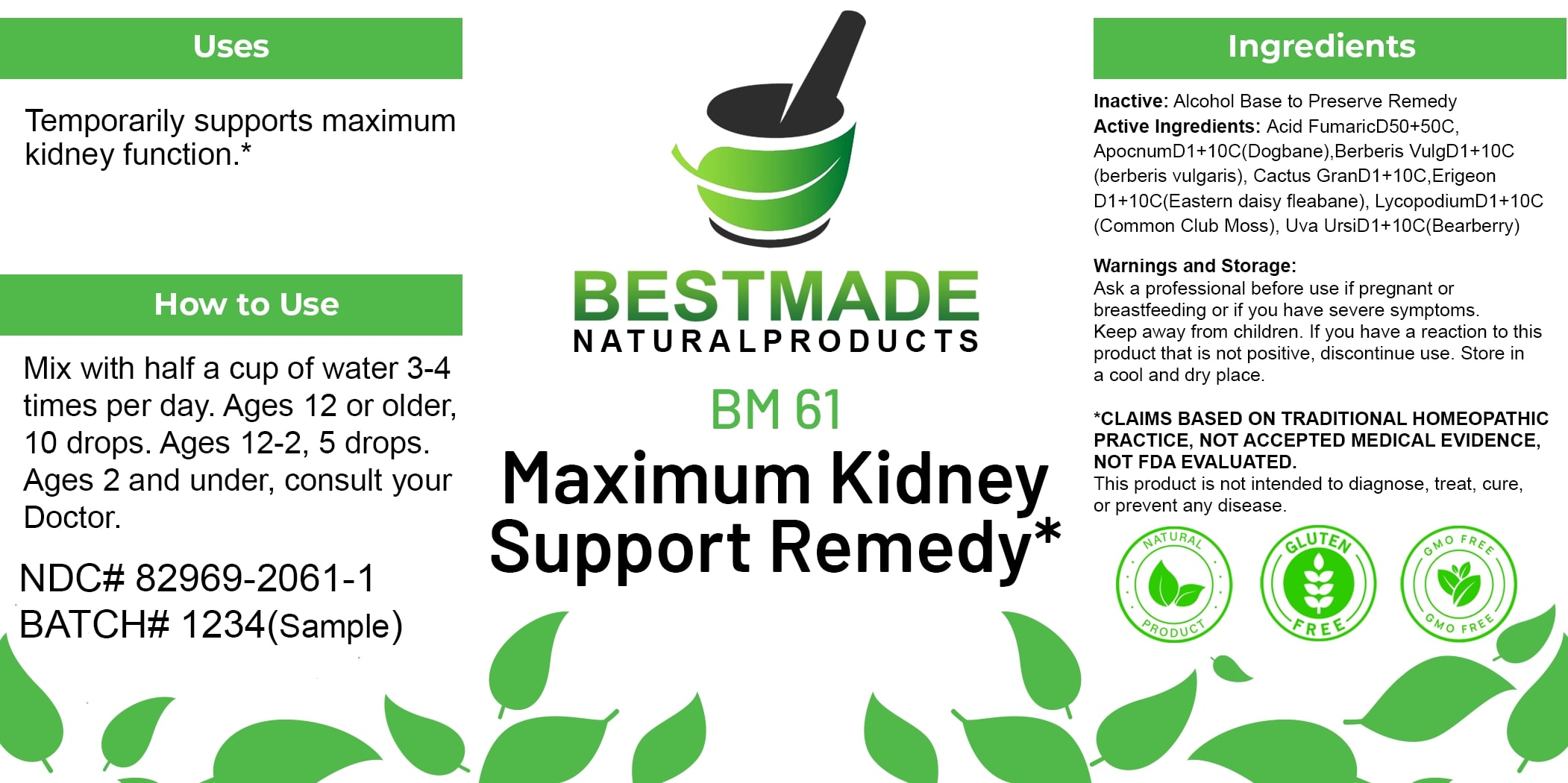 DRUG LABEL: Bestmade Natural Products BM61
NDC: 82969-2061 | Form: LIQUID
Manufacturer: Bestmade Natural Products
Category: homeopathic | Type: HUMAN OTC DRUG LABEL
Date: 20250124

ACTIVE INGREDIENTS: APOCYNUM CANNABINUM ROOT 10 [hp_C]/10 [hp_C]; BERBERIS VULGARIS ROOT BARK 10 [hp_C]/10 [hp_C]; LYCOPODIUM CLAVATUM SPORE 10 [hp_C]/10 [hp_C]; ARCTOSTAPHYLOS UVA-URSI LEAF 10 [hp_C]/10 [hp_C]; SELENICEREUS GRANDIFLORUS STEM 10 [hp_C]/10 [hp_C]; ERIGERON CANADENSIS 10 [hp_C]/10 [hp_C]; FUMARIC ACID 10 [hp_C]/10 [hp_C]
INACTIVE INGREDIENTS: ALCOHOL 10 [hp_C]/10 [hp_C]

BM61 Maximum Kidney Support Remedy*

DOSAGE AND ADMINISTRATION

How to Use

Mix with half a cup of water 3-4 times per day. Ages 12 or older, 10 drops. Ages 12-2, 5 drops. Ages 2 and under, consult your Doctor.

INACTIVE INGREDIENT

Ingredients

Inactive: Alcohol Base to Preserve Remedy

ACTIVE INGREDIENT

Active Ingredients: Acid Fumaric D50+50C, Apocnum D1+10C (Dogbane), Berberis Vulg D1+10C (Berberis vulgaris), Cactus Gran D1+10C, Erigeon D1+10C (Eastern daisy fleabane), Lycopodium D1+10C (Common Club Moss), Uva Ursi D1+10C (Bearberry)

Uses

Temporarily supports maximum kidney function.*

*CLAIMS BASED ON TRADITIONAL HOMEOPATHIC PRACTICE, NOT ACCEPTED MEDICAL EVIDENCE. NOT FDA EVALUATED.

This product is not intended to diagnose, treat, cure, or prevent any disease.

Uses

Temporarily supports maximum kidney function.*

*CLAIMS BASED ON TRADITIONAL HOMEOPATHIC PRACTICE, NOT ACCEPTED MEDICAL EVIDENCE. NOT FDA EVALUATED.

This product is not intended to diagnose, treat, cure, or prevent any disease.

KEEP OUT OF REACH OF CHILDREN

Warnings and Storage:

Ask a professional before use if pregnant or breastfeeding or if you have severe symptoms. Keep away from children. If you have a reaction to this product that is not positive, discontinue use. Store in a cool and dry place.

Warnings and Storage:

Ask a professional before use if pregnant or breastfeeding or if you have severe symptoms. Keep away from children. If you have a reaction to this product that is not positive, discontinue use. Store in a cool and dry place.

*CLAIMS BASED ON TRADITIONAL HOMEOPATHIC PRACTICE, NOT ACCEPTED MEDICAL EVIDENCE. NOT FDA EVALUATED.

This product is not intended to diagnose, treat, cure, or prevent any disease.

Entire package label